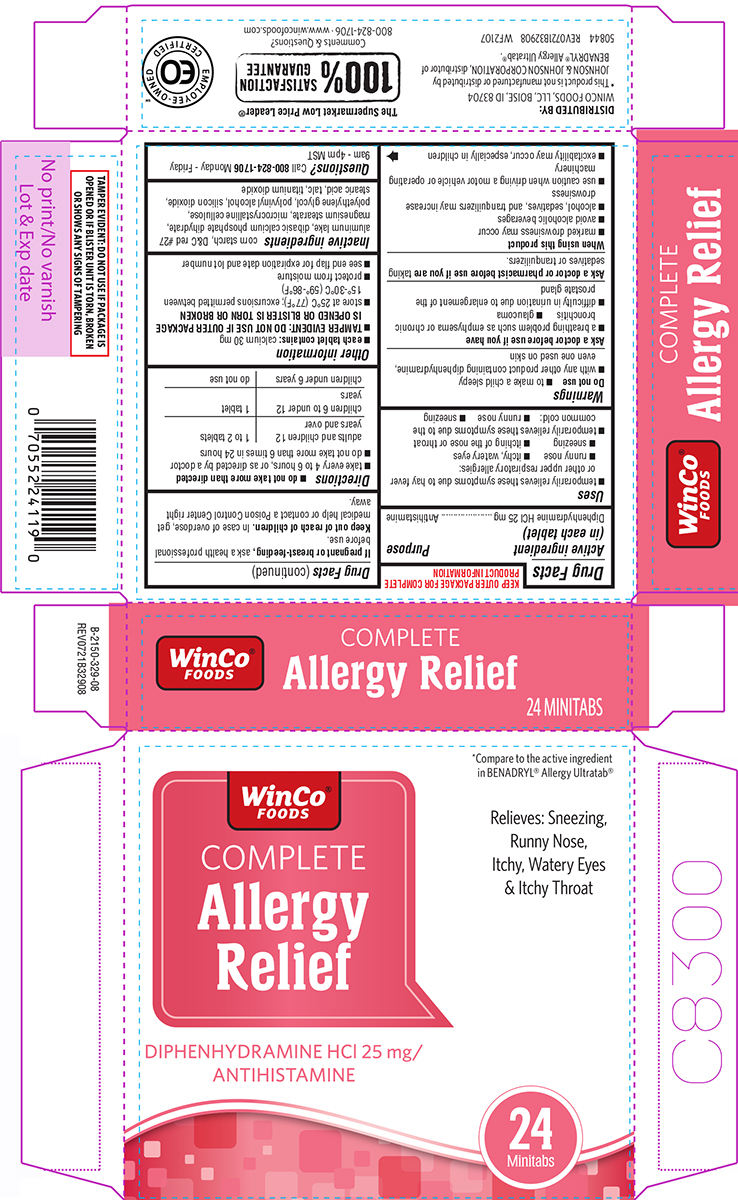 DRUG LABEL: Allergy Relief
NDC: 67091-200 | Form: TABLET, FILM COATED
Manufacturer: WinCo Foods, LLC
Category: otc | Type: HUMAN OTC DRUG LABEL
Date: 20251112

ACTIVE INGREDIENTS: DIPHENHYDRAMINE HYDROCHLORIDE 25 mg/1 1
INACTIVE INGREDIENTS: STARCH, CORN; D&C RED NO. 27 ALUMINUM LAKE; DIBASIC CALCIUM PHOSPHATE DIHYDRATE; MAGNESIUM STEARATE; MICROCRYSTALLINE CELLULOSE; POLYETHYLENE GLYCOL, UNSPECIFIED; POLYVINYL ALCOHOL, UNSPECIFIED; SILICON DIOXIDE; STEARIC ACID; TALC; TITANIUM DIOXIDE

Winco 44-329

Active ingredient (in each tablet)

Diphenhydramine HCl 25 mg

Purpose

Antihistamine

Uses

- temporarily relieves these symptoms due to hay fever or other upper respiratory allergies:
  - itchy, watery eyes
  - runny nose
  - sneezing
  - itching of the nose or throat
- temporarily relieves these symptoms due to the common cold:
  - runny nose
  - sneezing

Warnings

Do not use

- to make a child sleepy
- with any other product containing diphenhydramine, even one used on skin

Ask a doctor before use if you have

- a breathing problem such as emphysema or chronic bronchitis
- glaucoma
- difficulty in urination due to enlargement of the prostate gland

Ask a doctor or pharmacist before use if you are

taking sedatives or tranquilizers.

When using this product

- marked drowsiness may occur
- avoid alcoholic beverages
- alcohol, sedatives, and tranquilizers may increase drowsiness
- use caution when driving a motor vehicle or operating machinery
- excitability may occur, especially in children

If pregnant or breast-feeding,

ask a health professional before use.

Keep out of reach of children.

In case of overdose, get medical help or contact a Poison Control Center right away.

Directions

- do not take more than directed
- take every 4 to 6 hours, or as directed by a doctor
- do not take more than 6 times in 24 hours

adults and children 12 years and over | 1 to 2 tablets
children 6 to under 12 years | 1 tablet
children under 6 years | do not use

Other information

- each tablet contains: calcium 30 mg
- TAMPER EVIDENT: DO NOT USE IF OUTER PACKAGE IS OPENED OR BLISTER IS TORN OR BROKEN
- store at 25ºC (77ºF); excursions permitted between 15º-30ºC (59º-86ºF)
- protect from moisture
- see end flap for expiration date and lot number

Inactive ingredients

corn starch, D&C red #27 aluminum lake, dibasic calcium phosphate dihydrate, magnesium stearate, microcrystalline cellulose, polyethylene glycol, polyvinyl alcohol, silicon dioxide, stearic acid, talc, titanium dioxide

Questions?

Call 800-824-1706 Monday - Friday 9am - 4pm MST

Principal Display Panel

WinCo®
FOODS

*Compare to the active ingredient
in BENADRYL® Allergy Ultratab®

COMPLETE
Allergy
Relief

DIPHENHYDRAMINE HCl 25 mg/
ANTIHISTAMINE

Relieves: Sneezing,
Runny Nose,
Itchy, Watery Eyes
& Itchy Throat

24
Minitabs

DISTRIBUTED BY:
WINCO FOODS, LLC, BOISE, ID 83704

TAMPER EVIDENT: DO NOT USE IF PACKAGE IS
OPENED OR IF BLISTER UNIT IS TORN, BROKEN
OR SHOWS ANY SIGNS OF TAMPERING

*This product is not manufactured or distributed by
JOHNSON & JOHNSON CORPORATION, distributor of
BENADRYL® Allergy Ultratab®.

50844 REV0721B32908 WF2107

The Supermarket Low Price Leader®

100%
SATISFACTION
GUARANTEE
Comments & Questions?
800-824-1706 www.wincofoods.com

EO
EMPLOYEE-OWNED
CERTIFIED

Winco B-2150-329-08 REV0721B